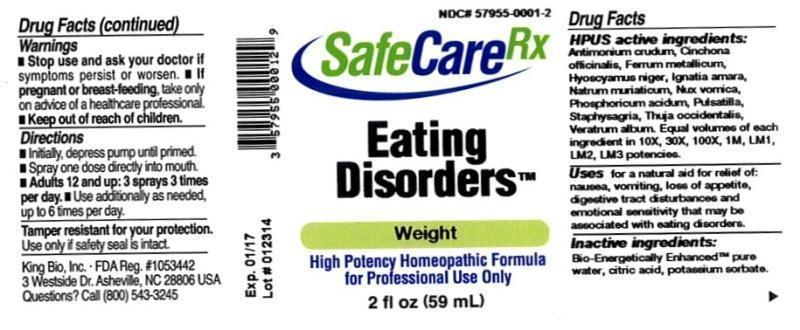 DRUG LABEL: Eating Disorders
NDC: 57955-0001 | Form: LIQUID
Manufacturer: King Bio Inc
Category: homeopathic | Type: HUMAN OTC DRUG LABEL
Date: 20140417

ACTIVE INGREDIENTS: ANTIMONY TRISULFIDE 10 [hp_X]/59 mL; CINCHONA OFFICINALIS BARK 10 [hp_X]/59 mL; IRON 10 [hp_X]/59 mL; HYOSCYAMUS NIGER 10 [hp_X]/59 mL; STRYCHNOS IGNATII SEED 10 [hp_X]/59 mL; SODIUM CHLORIDE 10 [hp_X]/59 mL; STRYCHNOS NUX-VOMICA SEED 10 [hp_X]/59 mL; PHOSPHORIC ACID 10 [hp_X]/59 mL; PULSATILLA VULGARIS 10 [hp_X]/59 mL; DELPHINIUM STAPHISAGRIA SEED 10 [hp_X]/59 mL; THUJA OCCIDENTALIS LEAFY TWIG 10 [hp_X]/59 mL; VERATRUM ALBUM ROOT 10 [hp_X]/59 mL
INACTIVE INGREDIENTS: WATER; CITRIC ACID MONOHYDRATE; POTASSIUM SORBATE

Eating Disorders™

ACTIVE INGREDIENT

Drug Facts__________________________________________________________________________________________________________

HPUS active ingredients: Antimonium crudum, Cinchona officinalis, Ferrum metallicum, Hyoscyamus niger, Ignatia amara, Natrum muriaticum, Nux vomica, Phosphoricum acidum, Pulsatilla, Staphysagria, Thuja occidentalis, Veratrum album. Equal volumes of each ingredient in 10X, 30X, 100X, 1M, LM1, LM2, LM3 potencies.

INDICATIONS AND USAGE

Uses for a natural aid for relief of: nausea, vomiting, loss of appetite, digestive tract disturbances and emotional sensitivity that may be associated with eating disorders.

Inactive Ingredients:

Bio-Energetically Enhanced™ pure water, citric acid and potassium sorbate.

Warnings

- Stop use and ask your doctor if symptoms persist or worsen.
- If pregnant or breast-feeding, take only on advice of a healthcare professional.

- Keep out of reach of children.

Directions

- Initially, depress pump until primed.
- Spray one dose directly into mouth.
- Adults 12 and up: 3 sprays 3 times per day.
- Use additionally as needed, up to 6 times per day.

OTHER SAFETY INFORMATION

Tamper resistant for your protection. Use only if safety seal is intact.

PURPOSE

Uses for a natural aid for relief of: nausea, vomiting, loss of appetite, digestive tract disturbances and emotional sensitivity that may be associated with eating disorders.